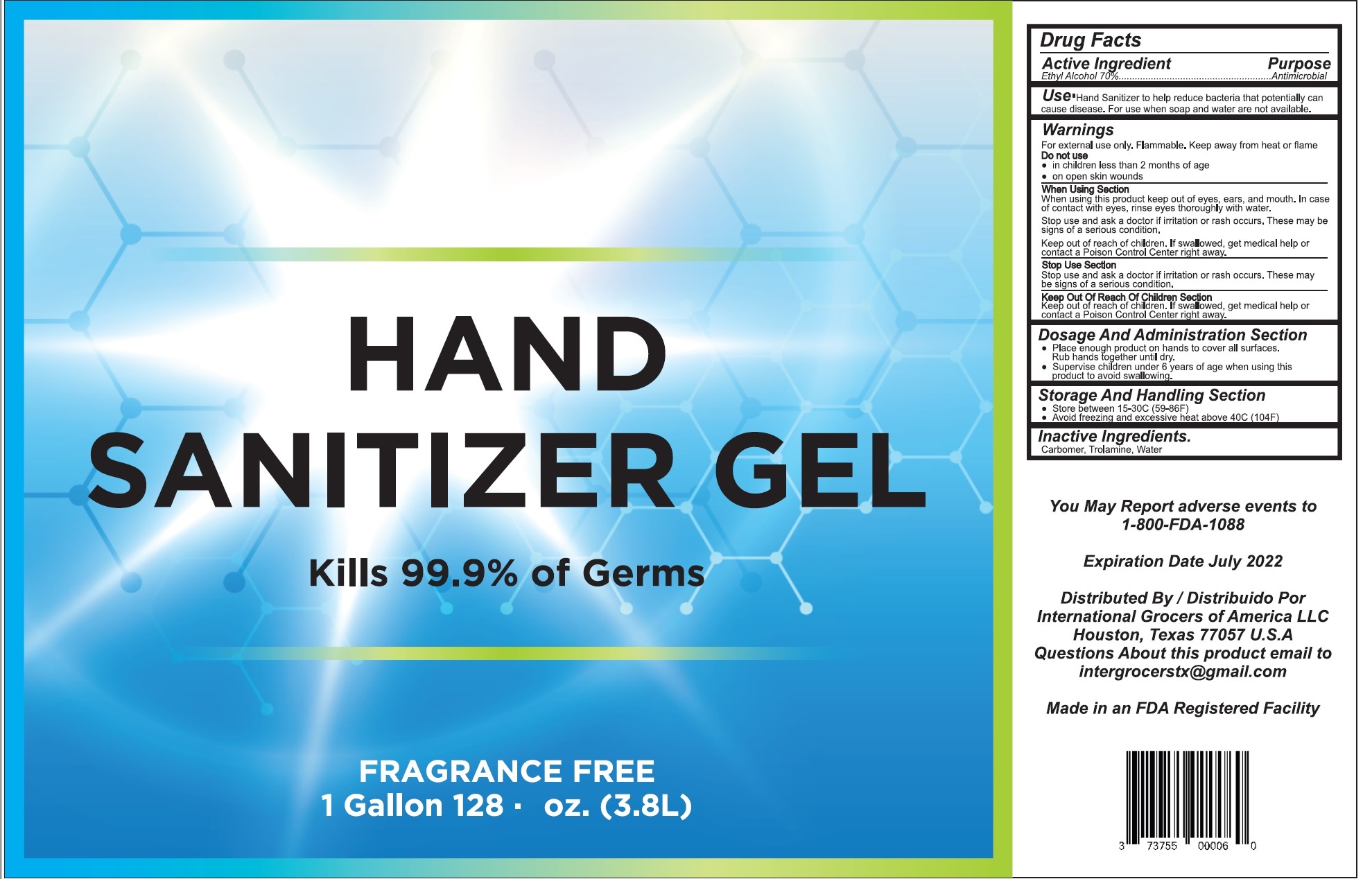 DRUG LABEL: AP Hand Sanitizer
NDC: 77287-200 | Form: GEL
Manufacturer: International Grocers of America LLC
Category: otc | Type: HUMAN OTC DRUG LABEL
Date: 20200716

ACTIVE INGREDIENTS: ALCOHOL 0.7 mL/1 mL
INACTIVE INGREDIENTS: CARBOMER HOMOPOLYMER, UNSPECIFIED TYPE 0.0025 mL/1 mL; TROLAMINE 0.004 mL/1 mL; WATER 0.289 mL/1 mL

Hand Sanitizer Gel

70% Alcohol

1 Gallon (3.8L)

Active Ingredient(s)

Alcohol 70% v/v. Purpose: Antimicrobial

Purpose

Antimicrobial, Hand Sanitizer Gel

Use

Hand Sanitizer to help reduce bacteria that potentially can cause disease. For use when soap and water are not available.

Warnings

For external use only. Flammable. Keep away from heat or flame

Do not use

- in children less than 2 months of age
- on open skin wounds

When using this product keep out of eyes, ears, and mouth. In case of contact with eyes, rinse eyes thoroughly with water.
Stop use and ask a doctor if irritation or rash occurs. These may be signs of a serious condition.
Keep out of reach of children. If swallowed, get medical help or contact a Poison Control Center right away.

Stop use and ask a doctor if irritation or rash occurs. These may be signs of a serious condition.

Keep out of reach of children. If swallowed, get medical help or contact a Poison Control Center right away.

Directions

- Place enough product on hands to cover all surfaces. Rub hands together until dry.
- Supervise children under 6 years of age when using this product to avoid swallowing.

Other information

- Store between 15-30C (59-86F)
- Avoid freezing and excessive heat above 40C (104F)

Inactive ingredients

CARBOMER, TROLAMINE, WATER

RECENT MAJOR CHANGES

HAND SANITIZER GEL

Package Label - Principal Display Panel

Hand Sanitizer Gel

Eliminates 99.99% of Germs

1 Gallon (3.8L)